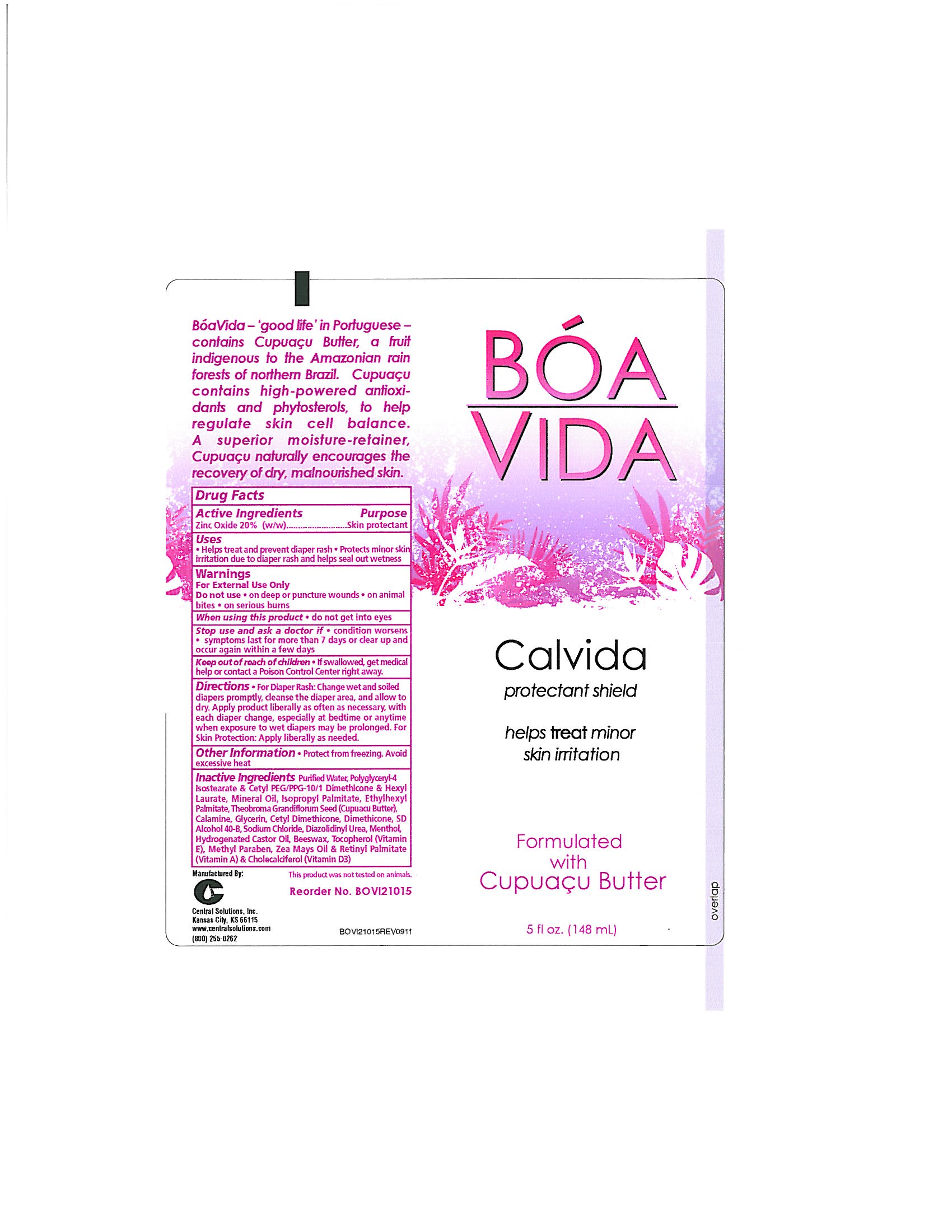 DRUG LABEL: BOA VIDA Calvida
NDC: 62654-145 | Form: CREAM
Manufacturer: Central Solutions Inc
Category: otc | Type: HUMAN OTC DRUG LABEL
Date: 20241209

ACTIVE INGREDIENTS: ZINC OXIDE 20 g/100 mL
INACTIVE INGREDIENTS: WATER; POLYGLYCERYL-4 ISOSTEARATE; HEXYL LAURATE; MINERAL OIL; ISOPROPYL PALMITATE; ETHYLHEXYL PALMITATE; THEOBROMA GRANDIFLORUM SEED; GLYCERIN; DIMETHICONE; SODIUM CHLORIDE; DIAZOLIDINYL UREA; MENTHOL; HYDROGENATED CASTOR OIL; YELLOW WAX; TOCOPHEROL; METHYLPARABEN; CORN OIL; VITAMIN A PALMITATE; CHOLECALCIFEROL

Drug Facts 62654-145

Active Ingredients

Zinc Oxide 20% (w/w)

Purpose

Skin protectant

Uses

Helps treat and prevent diaper rash

Protects minor skin irritation due to diaper rash and helps seal out wetness

Warnings

For External Use Only

Do not use

on deep or puncture wounds

on animal bites

on serious burns

When using this product

do not get into eyes

Stop use and ask a doctor if

condition worsens

symptoms last more than 7 days or clear up and occur again within a few days

Keep out of reach of children

If swallowed, get medical help or contact a Poison Control Center right away.

Directions

For Diaper Rash: Change wet and soiled diapers promptly, cleanse the diaper area, and allow to dry.

Apply product liberally as often as necessary, with each diaper change, especially at bedtime or anytime when exposure to wet diapers may be prolonged.

For Skin Protection: Apply liberally as needed.

Other Information

Protect from freezing.

Avoid excessive heat

Inactive Ingredients

Purified Water, Polyglyceryl-4 Isostearate and Cetyl PEG/PPG-10/1 Dimethicone and Hexyl Laurate, Mineral Oil, Isopropyl Palmitate, Ethylhexyl Palmitate, Theobroma Grandiflorum Seed (Cupuacu Butter), Calamine, Glycerin, Cetyl Dimethicone, Dimethicone, SD Alcohol 40-B, Sodium Chloride, Diazolidinyl Urea, Menthol, Hydrogenated Castor Oil, Beeswax, Tocopherol (Vitamin E), Methyl Paraben, Zea Mays Oil and Retinyl Palmitate (Vitamin A) and Cholecalciferol (Vitamin D3)

PACKAGE LABEL

BOA

VIDA

Calvida

protectant shield

helps treat minor

skin irritation

Formulated

with

Cupuacu Butter

5 fl oz. (148 mL)